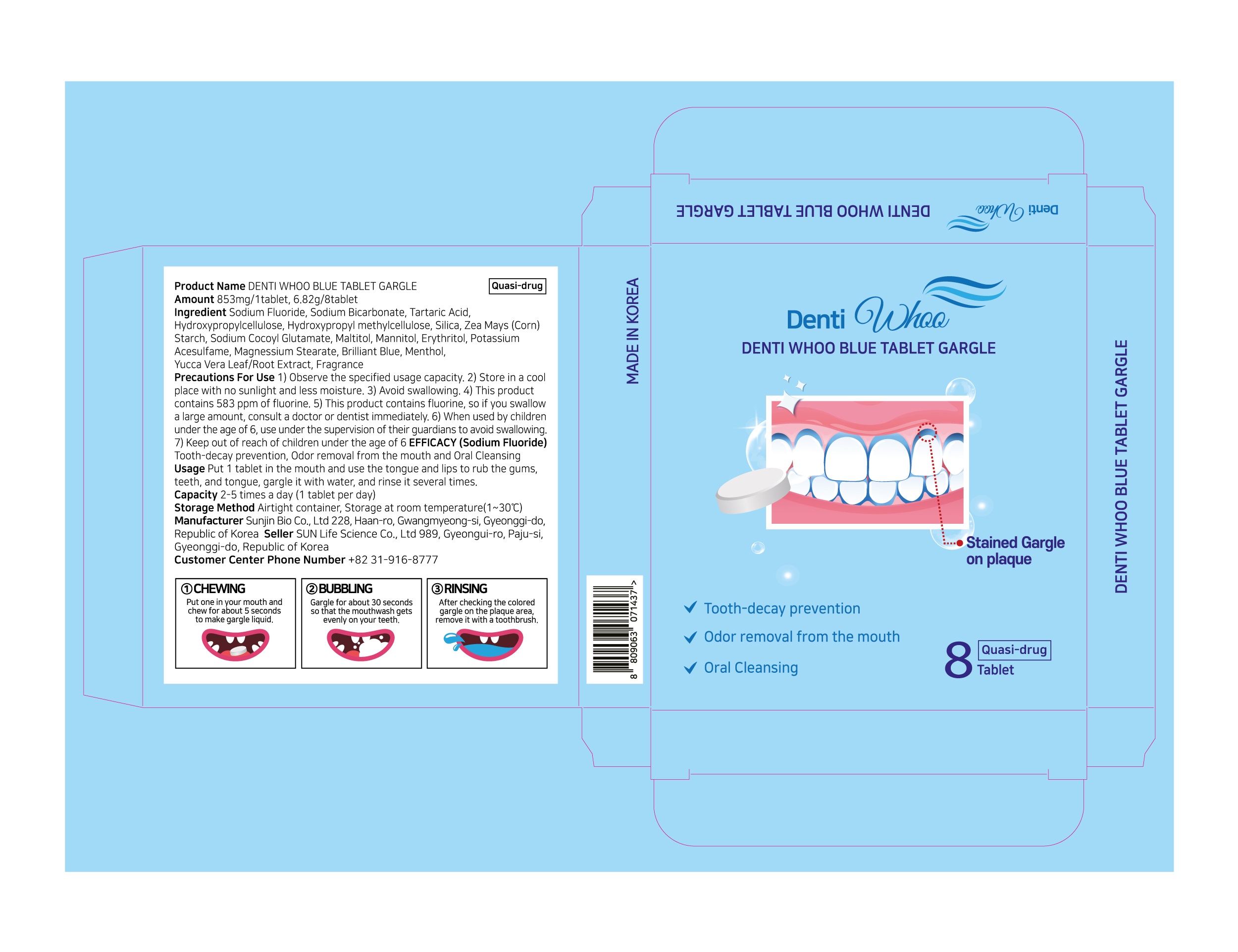 DRUG LABEL: DENTI WHOO BLUE TABLETGARGLE
NDC: 86157-0014 | Form: TABLET
Manufacturer: SUN LIFE SCIENCE CO LTD
Category: otc | Type: HUMAN OTC DRUG LABEL
Date: 20220517

ACTIVE INGREDIENTS: SODIUM FLUORIDE 1.10037 g/1 1
INACTIVE INGREDIENTS: TARTARIC ACID; MALTITOL; SODIUM BICARBONATE

ACTIVE INGREDIENT

Sodium Fluoride

INACTIVE INGREDIENT

Sodium Bicarbonate
Tartaric Acid
Hydroxypropylcellulose
Hydroxypropyl methylcellulose
Silica
Zea Mays (Corn) Starch
Sodium Cocoyl Glutamate
Maltitol
Mannitol
Erythritol
Potassium Acesulfame
Magnessium Stearate
Brilliant Blue
Menthol
Yucca Vera Leaf/Root Extract

fragrance

PURPOSE

Tooth-decay prevention, Odor removal from the mouth and Oral Cleansing

Keep out of reach of children

INDICATIONS AND USAGE

USAGE : Put 1 tablet in the mouth and use the tongue and lips to rub the gums, teeth, and tongue, gargle it with water, and rinse it several times

WARNINGS

1) Observe the specified usage capacity.
2) Store in a cool place with no sunlight and less moisture.
3) Avoid swallowing.
4) This product contains 583 ppm of fluorine.
5) This product contains fluorine, so if you swallow a large amount, consult a doctor or dentist
immediately.
6) When used by children under the age of 6, use under the supervision of their guardians to
avoid swallowing.
7) Keep out of reach of children under the age of 6

DOSAGE AND ADMINISTRATION

For dental use only